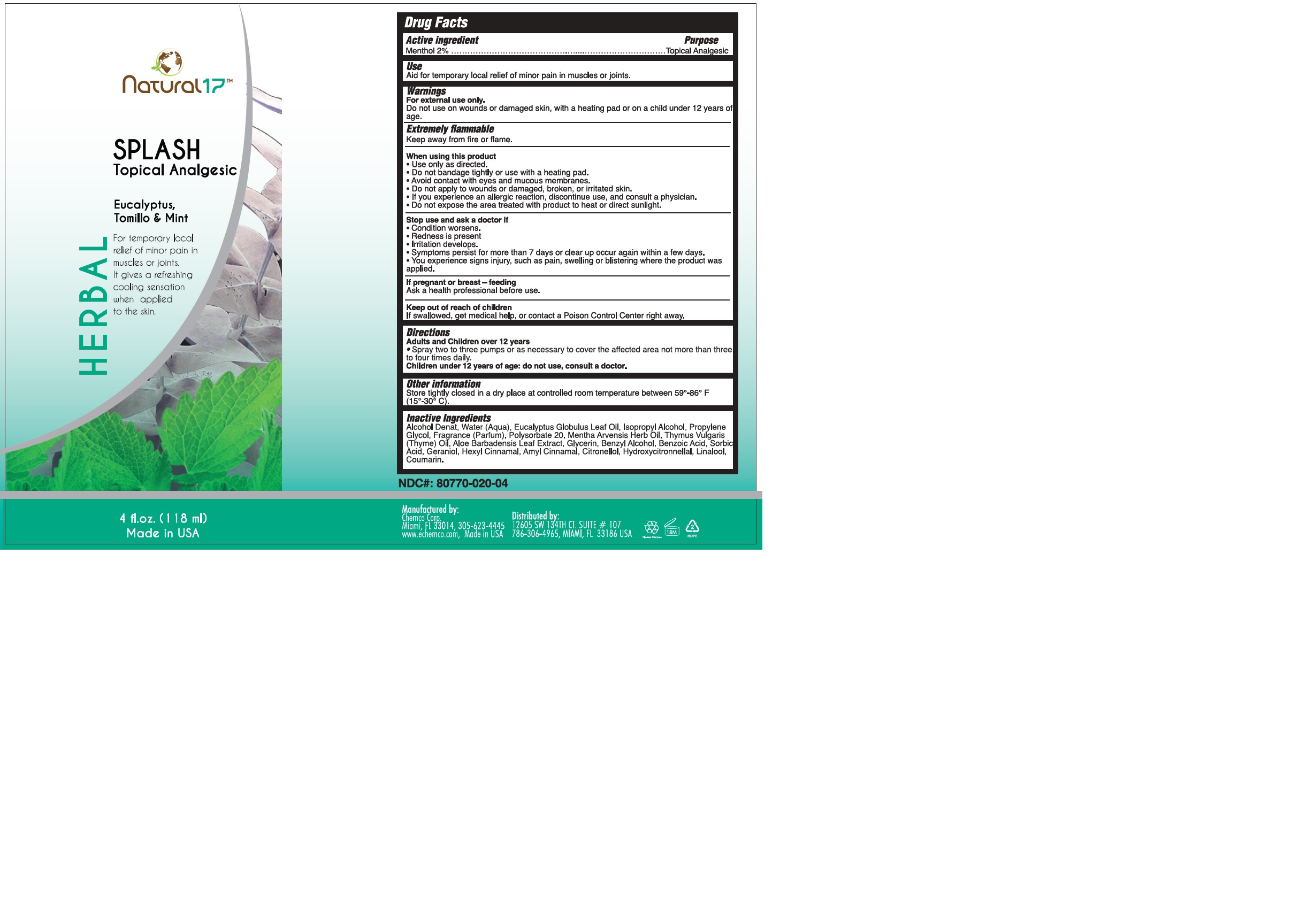 DRUG LABEL: NATURAL 17 HERBAL SPLASH
NDC: 80770-020 | Form: SPRAY
Manufacturer: NATURAL 17
Category: otc | Type: HUMAN OTC DRUG LABEL
Date: 20241122

ACTIVE INGREDIENTS: MENTHOL 1.7 g/100 mL
INACTIVE INGREDIENTS: POLYSORBATE 20; HYDROXYCITRONELLAL; WATER; ISOPROPYL ALCOHOL; GERANIOL; LINALOOL, (+)-; COUMARIN; EUCALYPTUS OIL; .ALPHA.-AMYLCINNAMALDEHYDE; PROPYLENE GLYCOL; GLYCERIN; .BETA.-CITRONELLOL, (R)-; ALCOHOL; BENZYL ALCOHOL; BENZOIC ACID; SORBIC ACID; .ALPHA.-HEXYLCINNAMALDEHYDE; MENTHA ARVENSIS LEAF OIL; ALOE VERA LEAF; THYME OIL

80770-020-04

ACTIVE INGREDIENT

Menthol …………………………………………...………………….……... 2%

PURPOSE

Topical Analgesic

INDICATIONS AND USAGE

For temporary relief of minor pains on muscles and joints.

WARNINGS

For external use only.

Do not use on wounds or damaged skin, with a heating pad or on a child under 12 years of age.

Extremely flammable

Keep away from fire or flame.

WHEN USING

Use only as directed.
Avoid contact with eyes and mucous membranes.
If you experience an allergic reaction, discontinue use, and consult a physician.

Do not expose the area treated with product to heat or direct sunlight.

Stop use and ask a doctor if

Condition worsens.
Redness is present.
Irritation develops.
Symptoms persist for more than 7 days or clear up occur again within a few days.

You experience signs injury, such as pain, swelling or blistering where the product was applied.

PREGNANCY OR BREAST FEEDING

Ask a health professional before use.

KEEP OUT OF REACH OF CHILDREN

If swallowed, get medical help, or contact a Poison Control Center right away.

Directions

Adults and Children over 12 years

Spray two to three pumps or as necessary to cover the affected area not more than three to four times daily.

Children under 12 years of age: do not use, consult a doctor.

Other information

Store tightly closed in a dry place at controlled room temperature between 59°-86° F (15°-30° C).

INACTIVE INGREDIENT

Alcohol Denat, Water (Aqua), Eucalyptus Globulus Leaf Oil, Isopropyl Alcohol, Propylene Glycol, Fragrance (Parfum), Polysorbate 20, Mentha Arvensis Herb Oil, Thymus Vulgaris (Thyme) Oil, Aloe Barbadensis Leaf Extract, Glycerin, Benzyl Alcohol, Benzoic Acid, Sorbic Acid, Geraniol, Hexyl Cinnamal, Amyl Cinnamal, Citronellol, Hydroxycitronnellal, Linalool, Coumarin.